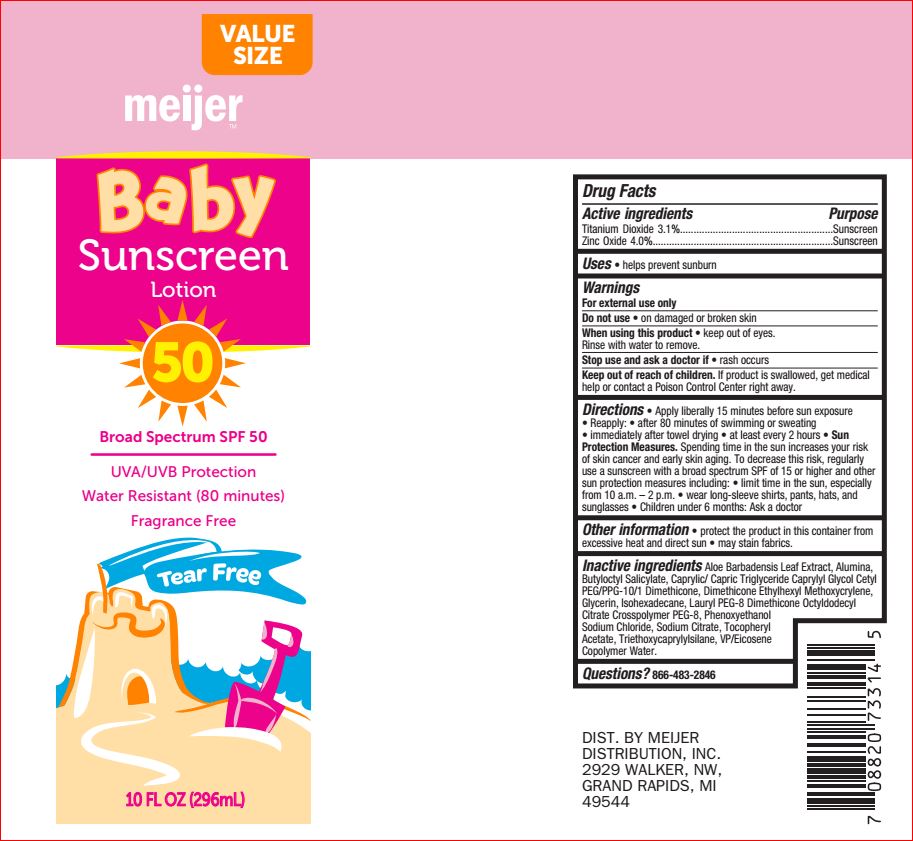 DRUG LABEL: Baby Sunscreen SPF 50
NDC: 41250-902 | Form: LOTION
Manufacturer: Meijer
Category: otc | Type: HUMAN OTC DRUG LABEL
Date: 20180629

ACTIVE INGREDIENTS: Titanium Dioxide 3.1 g/100 mL; Zinc Oxide 4 g/100 mL
INACTIVE INGREDIENTS: ALOE VERA LEAF; MEDIUM-CHAIN TRIGLYCERIDES; Caprylyl Glycol; Dimethicone; Ethylhexyl Methoxycrylene; Glycerin; Isohexadecane; POLYETHYLENE GLYCOL 400; Phenoxyethanol; Sodium Chloride; Sodium Citrate; .ALPHA.-TOCOPHEROL ACETATE; Triethoxycaprylylsilane; EICOSYL POVIDONE; Water

Drug Facts

Active ingredients Purpose
Titanium Dioxide 3.1%........................................................Sunscreen
Zinc Oxide 4.0%..................................................................Sunscreen

INDICATIONS AND USAGE

Uses • helps prevent sunburn

Warnings
For external use only
Do not use • on damaged or broken skin
When using this product • keep out of eyes.
Rinse with water to remove.
Stop use and ask a doctor if • rash occurs
Keep out of reach of children. If product is swallowed, get medical
help or contact a Poison Control Center right away.

DOSAGE AND ADMINISTRATION

Directions • Apply liberally 15 minutes before sun exposure
• Reapply: • after 80 minutes of swimming or sweating
• immediately after towel drying • at least every 2 hours • Sun
Protection Measures. Spending time in the sun increases your risk
of skin cancer and early skin aging. To decrease this risk, regularly
use a sunscreen with a broad spectrum SPF of 15 or higher and other
sun protection measures including: • limit time in the sun, especially
from 10 a.m. – 2 p.m. • wear long-sleeve shirts, pants, hats, and
sunglasses • Children under 6 months: Ask a doctor

Other information • protect the product in this container from
excessive heat and direct sun • may stain fabrics.

Inactive ingredients

Aloe Barbadensis Leaf Extract, Alumina,
Butyloctyl Salicylate, Caprylic/ Capric Triglyceride Caprylyl Glycol Cetyl
PEG/PPG-10/1 Dimethicone, Dimethicone Ethylhexyl Methoxycrylene,
Glycerin, Isohexadecane, Lauryl PEG-8 Dimethicone Octyldodecyl
Citrate Crosspolymer PEG-8, Phenoxyethanol
Sodium Chloride, Sodium Citrate, Tocopheryl
Acetate, Triethoxycaprylylsilane, VP/Eicosene
Copolymer Water.